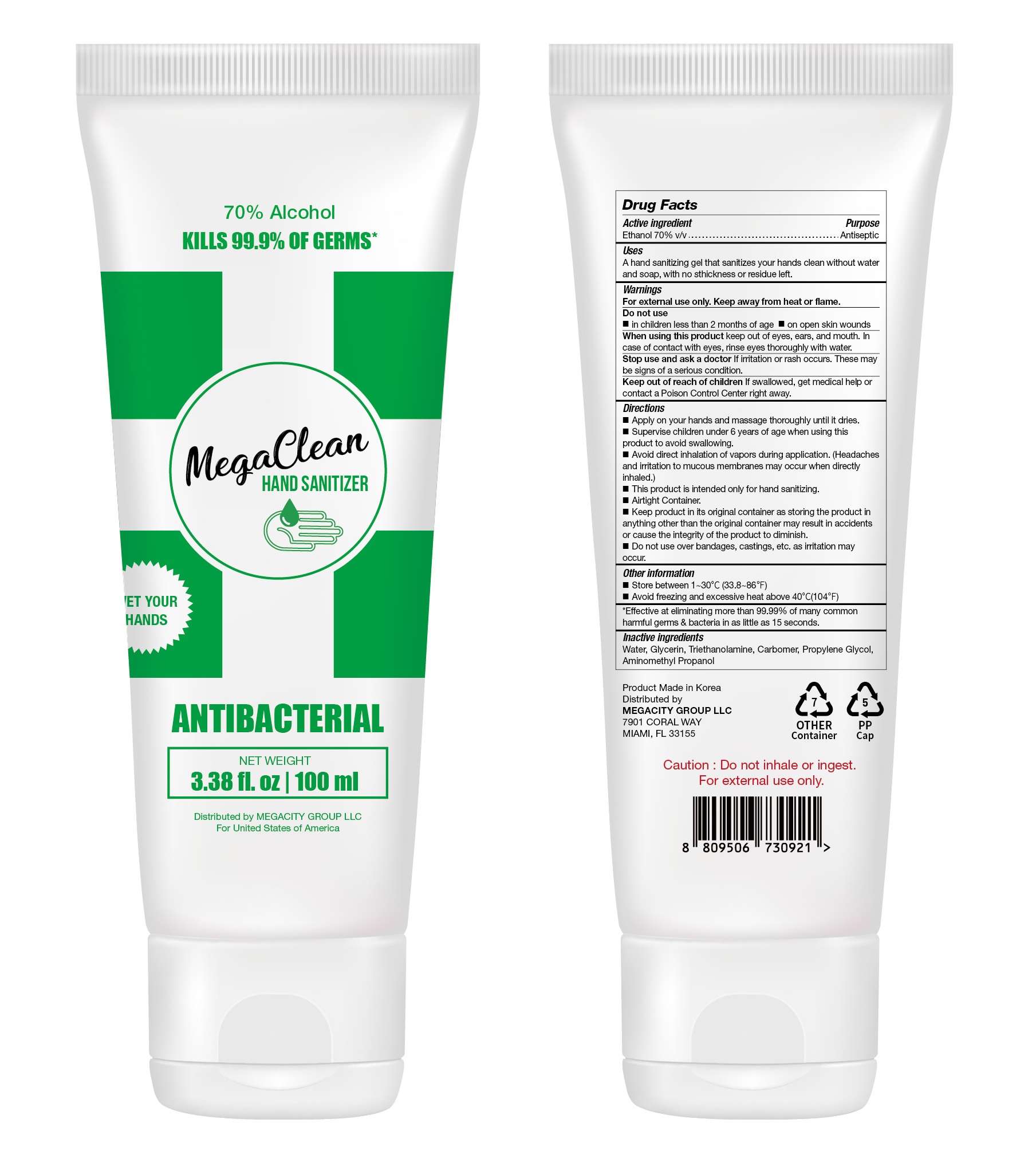 DRUG LABEL: MegaClean HAND SANITIZER
NDC: 77799-170 | Form: GEL
Manufacturer: MEGACITY GROUP LLC
Category: otc | Type: HUMAN OTC DRUG LABEL
Date: 20200531

ACTIVE INGREDIENTS: ALCOHOL 70 mL/100 mL
INACTIVE INGREDIENTS: AMINOMETHYLPROPANOL; GLYCERIN; WATER; PROPYLENE GLYCOL; TROLAMINE; CARBOMER HOMOPOLYMER, UNSPECIFIED TYPE

MegaClean HAND SANITIZER 100 mL : Tube : 77799-170-01